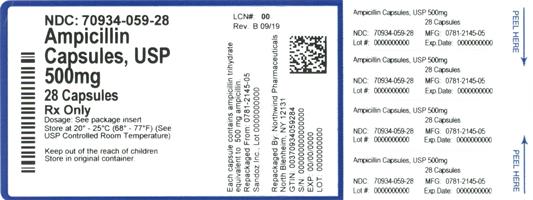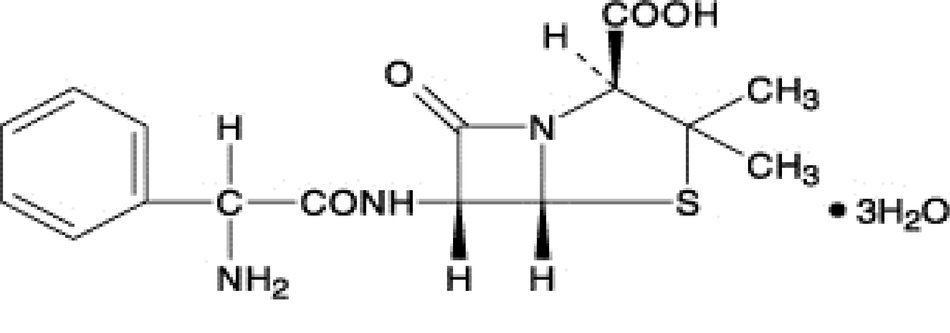 DRUG LABEL: Ampicillin
NDC: 70934-059 | Form: CAPSULE
Manufacturer: Denton Pharma, Inc. DBA Northwind Pharmaceuticals
Category: prescription | Type: HUMAN PRESCRIPTION DRUG LABEL
Date: 20200409

ACTIVE INGREDIENTS: AMPICILLIN TRIHYDRATE 500 mg/1 1
INACTIVE INGREDIENTS: AMMONIA; FERROSOFERRIC OXIDE; GELATIN; MAGNESIUM STEARATE; POTASSIUM HYDROXIDE; PROPYLENE GLYCOL; SHELLAC; TITANIUM DIOXIDE

Ampicillin Capsules, USP

To reduce the development of drug-resistant bacteria and maintain the effectiveness of ampicillin and other antibacterial drugs, ampicillin should be used only to treat or prevent infections that are proven or strongly suspected to be caused by bacteria.

DESCRIPTION

Ampicillin trihydrate is a semisynthetic penicillin derived from the basic penicillin nucleus, 6- aminopenicillanic acid. Ampicillin is designated chemically as (2S, 5 R, 6 R)-6-[(R)-2-Amino-2-phenylacetamido]-3,3- dimethyl-7-oxo-4-thia-1-azabicyclo [3.2.0] heptane-2- carboxylic acid. Its structural formula is:

Ampicillin Capsules, USP for oral administration provide ampicillin trihydrate equivalent to 250 mg and 500 mg ampicillin. Inactive ingredients: black iron oxide, gelatin, magnesium stearate, titanium dioxide, shellac, propylene glycol, ammonium hydroxide, and potassium hydroxide.

CLINICAL PHARMACOLOGY

Ampicillin is bactericidal at low concentrations and is clinically effective not only against the gram-positive organisms usually susceptible to penicillin G but also against a variety of gram-negative organisms. It is stable in the presence of gastric acid and is well absorbed from the gastrointestinal tract. It diffuses readily into most body tissues and fluids; however, penetration into the cerebrospinal fluid and brain occurs only with meningeal inflammation. Ampicillin is excreted largely unchanged in the urine; its excretion can be delayed by concurrent administration of probenecid which inhibits the renal tubular secretion of ampicillin. In blood serum, ampicillin is the least bound of all the penicillins; an average of about 20 percent of the drug is bound to plasma proteins as compared to 60 to 90 percent of the other penicillins. The administration of 500 mg dose of ampicillin capsules results in an average peak blood serum level of approximately 3.0 mcg/mL.

Microbiology

Mechanism of Action

Ampicillin is similar to penicillin in its bactericidal action against susceptible bacteria during the stage of active multiplication. It acts through the inhibition of cell wall biosynthesis that leads to the death of the bacteria.

Mechanism of Resistance

Resistance to ampicillin is mediated primarily through enzymes called beta-lactamases that cleave the beta-lactam ring of ampicillin, rendering it inactive.

Antimicrobial Activity

Ampicillin has been shown to be active against most isolates of the following bacteria, both in vitro and in clinical infections, as described in the INDICATIONS AND USAGE section.

Gram-positive Bacteria

Enterococcus spp.

Staphylococcus spp. (non-penicillinase-producing)

Streptococcus pneumoniae

Streptococcus pyogenes

Viridans group streptococci

Gram-negative Bacteria

Escherichia coli

Haemophilus influenzae (non-penicillinase-producing)

Neisseria gonorrhoeae

Neisseria meningitidis

Proteus mirabilis

Salmonella spp.

Shigellaspp.

The following in vitro data are available, but their clinical significance is unknown. At least 90 percent of the following bacteria exhibit an in vitro minimum inhibitory concentration (MIC) less than or equal to 0.12 mcg/mL for ampicillin. However the efficacy of ampicillin in treating clinical infections due to these bacteria has not been established in adequate and well-controlled trials.

Gram-positive Bacteria

Bacillus anthracis

Corynebacteriumxerosis

Anaerobic Bacteria

Clostridium spp.

Susceptibility Test Methods

When available, the clinical microbiology laboratory should provide in vitro susceptibility test results for antimicrobial drugs used in local hospitals and practice areas to the physician as periodic reports that describe the susceptibility profile of nosocomial and community-acquired pathogens. These reports should aid the physician in selecting an antimicrobial drug product for treatment.

Dilution Techniques

Quantitative methods are used to determine antimicrobial minimum inhibitory concentrations (MICs). These MICs provide estimates of the susceptibility of bacteria to antimicrobial compounds. The MICs should be determined using a standardized test method^1,3 (broth and/or agar). The MIC values should be interpreted according to the criteria provided in Table 1.

Diffusion Techniques

Quantitative methods that require measurement of zone diameters can also provide reproducible estimates of the susceptibility of bacteria to antimicrobial compounds. The zone size provides an estimate of the susceptibility of bacteria to antimicrobial compounds. The zone size should be determined using a standardized test method.^2,3This procedure uses paper disks impregnated with 10 mcg ampicillin to test the susceptibility of bacteria to ampicillin. The disk diffusion interpretive criteria are provided in Table 1.

Susceptibility to ampicillin of Staphylococcus spp., may be inferred by testing penicillin.^3

Perform test(s) to detect beta-lactamase production on staphylococci for which the penicillin MICs are ≤ 0.12 mcg/mL or zone diameters are ≥ 29 mm before reporting isolates as penicillin susceptible. Rare isolates of staphylococci that contain genes for beta-lactamase production may appear negative by beta-lactamase tests.

Consequently, for serious infections requiring penicillin therapy, laboratories should perform MIC tests and beta-lactamase testing on all subsequent isolates from the same patient. PCR testing of the isolate for the blaZ beta-lactamase gene may be considered.^3

Susceptibility to ampicillin of Streptococcus pneumoniae (non-meningitis isolates), may be inferred by testing penicillin or oxacillin. Non-meningitis isolates with a penicillin MIC ≤0.06 mcg/mL or oxacillin zone size ≥20 mm can be considered susceptible to ampicillin.^3

TABLE 1: Susceptibility Test Interpretive Criteria for Ampicillin
Pathogen | Minimum Inhibitory Concentrations (mcg/mL) |  |  | Disk Diffusion (Zone diameters in mm)
 | S | I | R | S | I | R
Enterobacteriaceae | ≤8 | 16 | ≥32 | ≥17 | 14-16 | ≤13
Haemophilus influenzae [The majority of isolates of H. influenzaethat are resistant to ampicillin produce a TEM-type beta-lactamase. In most cases, a direct beta-lactamase test can provide a rapid means of detecting resistance to ampicillin. 3] | ≤1 | 2 | ≥4 | ≥22 | 19-21 | ≤18
Enterococcus [Penicillin or ampicillin resistance among enterococci due to beta-lactamase production has been reported very rarely. Penicillin or ampicillin resistance due to beta-lactamase production is not reliably detected with routine disk or dilution methods, but is detected using a direct, nitrocefin-based beta-lactamase test. Because of the rarity of beta-lactamase-positive enterococci, this test need not be performed routinely, but can be used in selected cases. A positive beta-lactamase test predicts resistance to penicillin as well as amino- and ureidopenicillins. 3] spp. | ≤8 | - | ≥16 | ≥17 | - | ≤16
Neisseria meningitidis | ≤0.12 | 0.25-1 | ≥2 | - | - | -
Viridans group streptococci | ≤0.25 | 0.5-4 | ≥8
Streptococcus pyogenes [Susceptibility testing of ampicillin need not be performed routinely because nonsusceptible isolates of beta-hemolytic streptococci are extremely rare, and have not been reported for S. pyogenes. If testing is performed, any beta-hemolytic streptococcus isolate that is found to be non-susceptible should be re-identified retested, and if confirmed, reported to the public health laboratory. 3] | ≤0.25 | - | - | ≥24 | - | -
S = Susceptible; I = Intermediate; R = Resistant

A report of Susceptible indicates that the antimicrobial is likely to inhibit growth of the pathogen if the antimicrobial drug reaches the concentration usually achievable at the site of infection. A report of Intermediate indicates that the result should be considered equivocal, and, if the microorganism is not fully susceptible to alternative, clinically feasible drugs, the test should be repeated. This category implies possible clinical applicability in body sites where the drug is physiologically concentrated. This category also provides a buffer zone that prevents small uncontrolled technical factors from causing major discrepancies in interpretation. A report of Resistant indicates that the antimicrobial is not likely to inhibit growth of the pathogen if the antimicrobial compound reaches the concentration usually achievable at the infection site; other therapy should be selected.

Quality Control

Standardized susceptibility test procedures require use of laboratory controls to monitor and ensure the accuracy and precision of supplies and reagents used in the assay, and the techniques of the individuals performing the test.^1,2,3 Standard Ampicillin powder should provide the following range of MIC values noted in Table 2. For the diffusion technique using the 10 mcg ampicillin disk, the criteria in Table 2 should be achieved.

TABLE 2: Acceptable Quality Control Ranges for Ampicillin^3
QC strain | Minimum Inhibitory Concentration (mcg/mL) | Zone Diameter (mm)
Escherichia coli ATCC* 25922 | 2 - 8 | 15 - 22
Enterococcus faecalis ATCC 29212 | 0.5 - 2
Haemophilus influenzae ATCC 49247 | 2 - 8 | 13 - 21
Klebsiellapneumoniae ATCC 700603 | >128
Staphylococcus aureus ATCC 29213 | 0.5 - 2
Staphylococcus aureus ATCC 25923 |  | 27 - 35
Streptococcus pneumoniae ATCC 49619 | 0.06 – 0.25 | 30 - 36
* ATCC = American Type Culture Collection

INDICATIONS AND USAGE

Ampicillin Capsules, USP are indicated in the treatment of infections caused by susceptible strains of the designated organism listed below:

INFECTIONS OF THE GENITOURINARY TRACT INCLUDING GONORRHEA: E. coli, P. mirabilis, enterococci, Shigella, S. typhosaand other Salmonella, and nonpenicillinase producing N. gonorrhoeae.

INFECTIONS OF THE RESPIRATORY TRACT: Nonpenicillinase- producing H. influenzaeand staphylococci, and streptococci including streptococcus pneumoniae.

INFECTIONS OF THE GASTROINTESTINAL TRACT:

Shigella, S. typhosa and other Salmonella, E. coli, P. mirabilis, and enterococci.

MENINGITIS: N. Meningitides.

To reduce the development of drug-resistant bacteria and maintain the effectiveness of ampicillin and other antibacterial drugs, ampicillin should be used only to treat or prevent infections that are proven or strongly suspected to be caused by susceptible bacteria. When culture and susceptibility information are available, they should be considered in selecting or modifying antibacterial therapy. In the absence of such data, local epidemiology and susceptibility patterns may contribute to the empiric selection of therapy.

Bacteriology studies to determine the causative organisms and their susceptibility to ampicillin should be performed. Therapy may be instituted prior to the results of susceptibility testing.

CONTRAINDICATIONS

A history of a previous hypersensitivity reaction to any of the penicillins is a contraindication. Ampicillin is also contraindicated in infections caused by penicillinase-producing organisms.

WARNINGS

SERIOUS AND OCCASIONAL FATAL HYPERSENSITIVITY (ANAPHYLACTOID) REACTIONS HAVE BEEN REPORTED IN PATIENTS ON PENICILLIN THERAPY. ALTHOUGH ANAPHYLAXIS IS MORE FREQUENT FOLLOWING PARENTERAL ADMINISTRATION, IT HAS OCCURRED IN PATIENTS ON ORAL PENICILLINS. THESE REACTIONS ARE MORE LIKELY TO OCCUR IN INDIVIDUALS WITH A HISTORY OF PENICILLIN HYPERSENSITIVITY AND/OR A HISTORY OF SENSITIVITY TO MULTIPLE ALLERGENS.

THERE HAVE BEEN REPORTS OF INDIVIDUALS WITH A HISTORY OF PENICILLIN HYPERSENSITIVITY WHO HAVE EXPERIENCED SEVERE HYPERSENSITIVITY REACTIONS WHEN TREATED WITH CEPHALOSPORINS. BEFORE INITIATING THERAPY WITH ANY PENICILLIN, CAREFUL INQUIRY SHOULD BE MADE CONCERNING PREVIOUS HYPERSENSITIVITY REACTIONS TO PENICILLINS, CEPHALOSPORINS, AND OTHER ALLERGENS. IF AN ALLERGIC REACTION OCCURS, THE DRUG SHOULD BE DISCONTINUED AND APPROPRIATE THERAPY INSTITUTED. SERIOUS ANAPHYLACTOID REACTIONS REQUIRE IMMEDIATE EMERGENCY TREATMENT WITH EPINEPHRINE. OXYGEN, INTRAVENOUS STEROIDS, AND AIRWAY MANAGEMENT, INCLUDING INTUBATION, SHOULD ALSO BE ADMINISTERED AS INDICATED.

Pseudomembranous colitis has been reported with nearly all antibacterial agents, including ampicillin, and may range in severity from mild to life-threatening. Therefore, it is important to consider this diagnosis in patients who present with diarrhea subsequent to the administration of antibacterial agents.

Treatment with antibacterial agents alters the normal flora of the colon and may permit overgrowth of clostridia. Studies indicate that a toxin produced by Clostridium difficile, is one primary cause of “antibiotic-associated colitis”.

After the diagnosis of pseudomembranous colitis has been established, therapeutic measures should be initiated. Mild cases of pseudomembranous colitis usually respond to drug discontinuation alone. In moderate to severe cases, consideration should be given to management with fluids and electrolytes, protein supplementation and treatment with an antibacterial drug clinically effective against C. difficile colitis.

PRECAUTIONS

General

Prolonged use of antibiotics may promote the overgrowth of nonsusceptible organisms, including fungi. Should superinfection occur, appropriate measures should be taken.

Patients with gonorrhea who also have syphilis should be given additional appropriate parenteral penicillin treatment.

Treatment with ampicillin does not preclude the need for surgical procedures, particularly in staphylococcal infections.

Prescribing ampicillin in the absence of a proven or strongly suspected bacterial infection or a prophylactic indication is unlikely to provide benefit to the patient and increases the risk of the development of drug-resistant bacteria.

Information For The Patient

1. The patient should inform the physician of any history of sensitivity to allergens, including previous hypersensitivity reactions to penicillins and cephalosporins (see WARNINGS).
2. The patient should discontinue ampicillin and contact the physician immediately if any side effect occurs (see WARNINGS).
3. Ampicillin should be taken with a full glass (8 oz) of water, one-half hour before or two hours after meals.
4. Diabetic patients should consult with the physician before changing diet or dosage of diabetes medication (see PRECAUTIONS–Drug/Laboratory Test Interactions).
5. Patients should be counseled that antibacterial drugs including ampicillin should only be used to treat bacterial infections. They do not treat viral infections (e.g., the common cold). When ampicillin is prescribed to treat a bacterial infection, patients should be told that although it is common to feel better early in the course of therapy, the medication should be taken exactly as directed. Skipping doses or not completing the full course of therapy may: (1) decrease the effectiveness of the immediate treatment, and (2) increase the likelihood that bacteria will develop resistance and will not be treatable by ampicillin or other antibacterial drugs in the future.

Laboratory Tests

In prolonged therapy, and particularly with high dosage regimens, periodic evaluation of the renal, hepatic, and hematopoietic systems is recommended.

In streptococcal infections, therapy, must be sufficient to eliminate the organism (10 days minimum); otherwise the sequelae of streptococcal disease may occur. Cultures should be taken following completion of treatment to determine whether streptococci have been eradicated.

Cases of gonococcal infection with a suspected lesion of syphilis should have darkfield examinations ruling out syphilis before receiving ampicillin. Patients who do not have suspected lesions of syphilis and are treated with ampicillin should have a follow-up serologic test for syphilis each month for four months to detect syphilis that may have been masked for treatment for gonorrhea.

Drug Interactions

When administered concurrently, the following drugs may interact with ampicillin.

ALLOPURINOL: Increased possibility of skin rash, particularly in hyperuricemic patients may occur.

BACTERIOSTATIC ANTIBIOTICS: Chloramphenicol, erythromycins, sulfonamides, or tetracyclines may interfere with the bactericidal effect of penicillins. This has been demonstrated in vitro; however, the clinical significance of this interaction is not well-documented.

ORAL CONTRACEPTIVES: May be less effective and increased breakthrough bleeding may occur.

PROBENECID: May decrease renal tubular secretion of ampicillin resulting in increased blood levels and/or ampicillin toxicity.

Drug/Laboratory Test Interactions

After treatment with ampicillin, a false-positive reaction for glucose in the urine may occur with copper sulfate tests (Benedict’s solution, Fehling’s solution, or Clinitest® tablets) but not with enzyme based tests such as Clinistix® and Tes-Tape®.

Carcinogenesis, Mutagenesis, Impairment of Fertility

Long-term studies in animals have not been performed to evaluate carcinogenesis, mutagenesis, or impairment of fertility in males or females.

Pregnancy

Teratogenic Effects

Category B

Reproduction studies in animals have revealed no evidence of impaired fertility or harm to the fetus due to penicillin. There are, however, no adequate and well-controlled studies in pregnant women. Because animal reproduction studies are not always predictive of human response, penicillin should be used during pregnancy only if clearly needed.

Labor and Delivery

Oral ampicillin-class antibiotics are poorly absorbed during labor. Studies in guinea pigs showed that intravenous administration of ampicillin slightly decreased the uterine tone and frequency of contractions, but moderately increased the height and duration of contractions. However, it is not known whether use of these drugs in humans during labor or delivery has immediate or delayed adverse effects on the fetus, prolongs the duration of labor, or increases the likelihood that forceps delivery or other obstetrical intervention or resuscitation of the newborn will be necessary.

Nursing Mothers

Ampicillin-class antibiotics are excreted in milk. Ampicillin used by nursing mothers may lead to sensitization of infants; therefore, a decision should be made whether to discontinue nursing or to discontinue ampicillin, taking into account the importance of the drug to the mother.

Pediatric Use

Penicillins are excreted primarily unchanged by the kidney; therefore, the incompletely developed renal function in neonates and young infants will delay the excretion of penicillin. Administration to neonates and young infants should be limited to the lowest dosage compatible with an effective therapeutic regimen (see DOSAGE AND ADMINISTRATION).

ADVERSE REACTIONS

As with other penicillins, it may be expected that untoward reactions will be essentially limited to sensitivity phenomena. They are more likely to occur in individuals who have previously demonstrated hypersensitivity to penicillin and in those with a history of allergy, asthma, hay fever, or urticaria.

The following adverse reactions have been reported as associated with the use of ampicillin:

GASTROINTESTINAL: glossitis, stomatitis, nausea, vomiting, enterocolitis, pseudomembranous colitis, and diarrhea. These reactions are usually associated with oral dosage forms of the drugs.

HYPERSENSITIVITY REACTIONS: An erythematous, mildly pruritic, maculopapular skin rash has been reported fairly frequently . The rash, which usually does not develop within the first week of therapy, may cover the entire body including the soles, palms, and oral mucosa. The eruption usually disappears in three to seven days. Other hypersensitivity reactions that have been reported are: skin rash, pruritus, urticaria, erythema multiforme, and an occasional case of exfoliative dermatitis. Anaphylaxis is the most serious reaction experienced and has usually been associated with the parenteral dosage form of the drug.

NOTE: Urticaria, other skin rashes, and serum sickness-like reactions may be controlled by antihistamines, and, if necessary, systemic corticosteroids. Whenever such reactions occur, ampicillin should be discontinued unless, in the opinion of the physician, the condition being treated is life-threatening, and amenable only to ampicillin therapy. Serious anaphylactoid reactions require emergency measures (see WARNINGS).

LIVER: Moderate elevation in serum glutamic oxaloacetic transaminase (SGOT) has been noted, but the significance of this finding is unknown.

HEMIC AND LYMPHATIC SYSTEMS: Anemia, thrombocytopenia, thrombocytopenic purpura, eosinophilia, leukopenia, and agranulocytosis have been reported during therapy with penicillins. These reactions are usually reversible on discontinuation of therapy and are believed to be hypersensitivity phenomena.

Other adverse reactions that have been reported with the use of ampicillin are laryngeal stridor and high fever. An occasional patient may complain of sore mouth or tongue as with any oral penicillin preparation.

OVERDOSAGE

In case of overdosage, discontinue medication, treat symptomatically and institute supportive measures as required. In patients with renal function impairment, ampicillin-class antibiotics can be removed by hemodialysis but not by peritoneal dialysis.

DOSAGE AND ADMINISTRATION

ADULTS AND CHILDREN WEIGHING OVER 20 KG:

For genitourinary or gastrointestinal tract infections other than gonorrhea in men and women, the usual dose is 500 mg qid in equally spaced doses; severe or chronic infections may require larger doses. For the treatment of gonorrhea in both men and women, a single oral dose of 3.5 grams of ampicillin administered simultaneously with 1 gram of probenecid is recommended. Physicians are cautioned to use no less than the above recommended dosage for the treatment of gonorrhea. Follow-up cultures should be obtained from the original site(s) of infection 7 to 14 days after therapy. In women, it is also desirable to obtain culture test-of-cure from both the endocervical and anal canals. Prolonged intensive therapy is needed for complications such as prostatitis and epididymitis.

For respiratory tract infections, the usual dose is 250 mg qid in equally spaced doses.

CHILDREN WEIGHING 20 KG OR LESS:

For genitourinary or gastrointestinal tract infections, the usual dose is 100 mg/kg/day total, qid in equally divided and spaced doses. For respiratory infections, the usual dose is 50 mg/kg/day total, in equally divided and spaced doses three to four times daily. Doses for children should not exceed doses recommended for adults.

ALL PATIENTS, IRRESPECTIVE OF AGE AND WEIGHT:

Larger doses may be required for severe or chronic infections. Although ampicillin is resistant to degradation by gastric acid, it should be administered at least one-half hour before or two hours after meals for maximal absorption. Except for the single dose regimen for gonorrhea referred to above, therapy should be continued for a minimum of 48 to 72 hours after the patient becomes asymptomatic or evidence of bacterial eradication has been obtained. In infections caused by hemolytic strains of streptococci, a minimum of 10 days’ treatment is recommended to guard against the risk of rheumatic fever of glomerulonephritis (see PRECAUTIONS–Laboratory Tests). In the treatment of chronic urinary or gastrointestinal infections, frequent bacteriologic and clinical appraisal is necessary during therapy and may be necessary for several months afterwards. Stubborn infections may require treatment for several weeks. Smaller doses than those indicated above should not be used.

HOW SUPPLIED

Ampicillin Capsules, USP: Each capsule, for oral administration, contains ampicillin trihydrate equivalent to 500 mg ampicillin, and are supplied as:

500 mg: white, opaque, hard gelatin capsules, imprinted in black ink GG 851/GG 851.

Bottles of 28 NDC 70934-059-28

STORAGE AND HANDLING

Store at 20° to 25°C (68° to 77°F) [see USP Controlled Room Temperature].

Dispense in a tight container.

REFERENCES

1. Clinical and Laboratory Standards Institute (CLSI). Methods for Dilution Antimicrobial Susceptibility Tests for Bacteria that Grow Aerobically; Approved Standard - Tenth Edition. CLSI document M07-A10, Clinical and Laboratory Standards Institute, 950 West Valley Road, Suite 2500, Wayne, Pennsylvania 19087, USA, 2015.
2. Clinical and Laboratory Standards Institute (CLSI). Performance Standards for Antimicrobial Disk Diffusion Susceptibility Tests; Approved Standard – Twelfth Edition. CLSI document M02-A12, Clinical and Laboratory Standards Institute, 950 West Valley Road, Suite 2500, Wayne, Pennsylvania 19087, USA, 2015.
3. Clinical and Laboratory Standards Institute (CLSI). Performance Standards for Antimicrobial Susceptibility Testing; Twenty-fifth Informational Supplement, CLSI document M100-S25. CLSI document M100-S25, Clinical and Laboratory Standards Institute, 950 West Valley Road, Suite 2500, Wayne, Pennsylvania 19087, USA, 2015.

Principal Display Panel

NDC: 70934-059-28